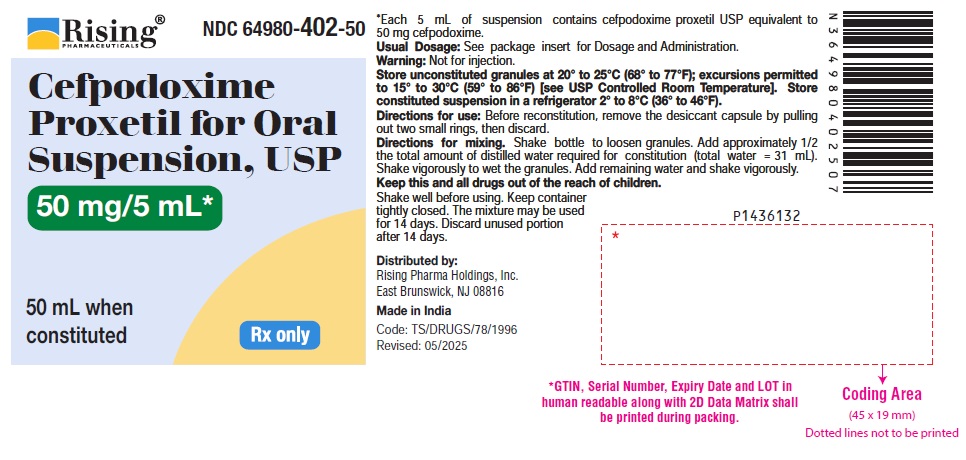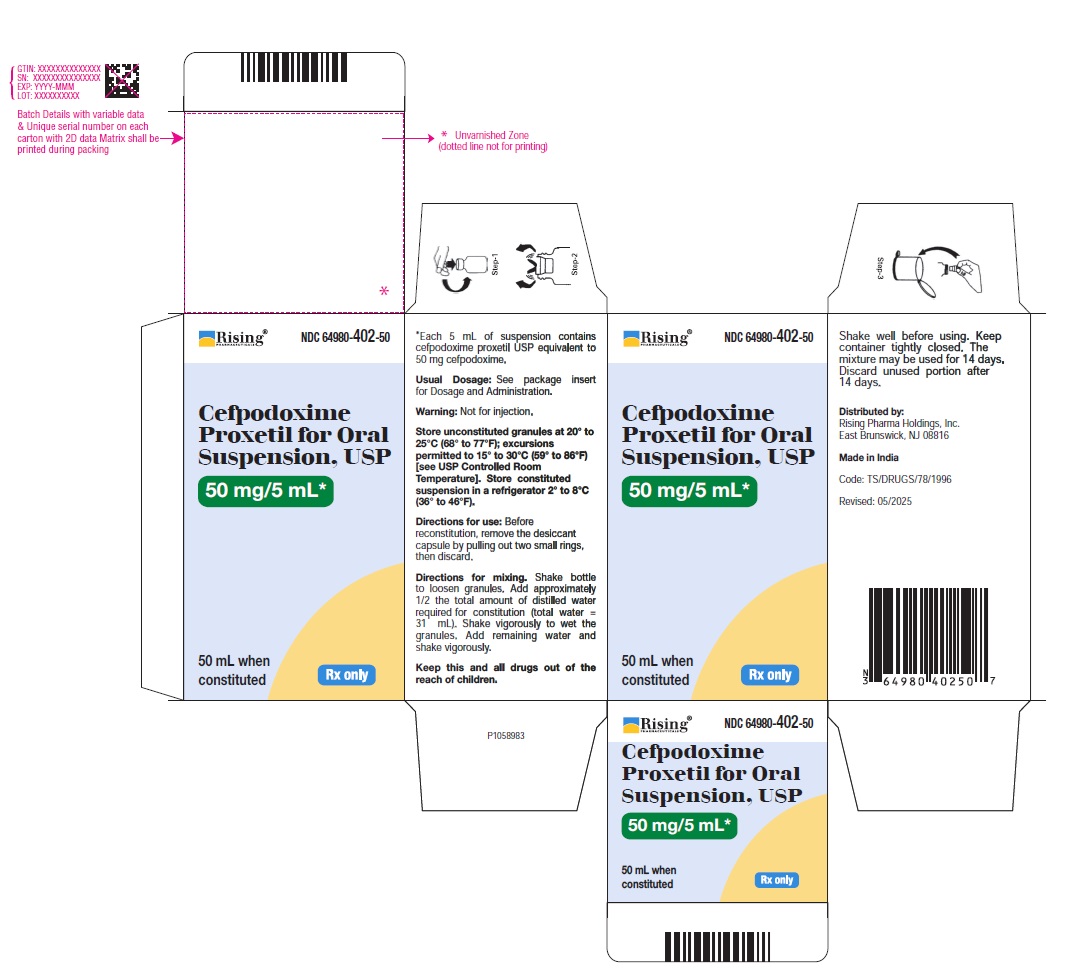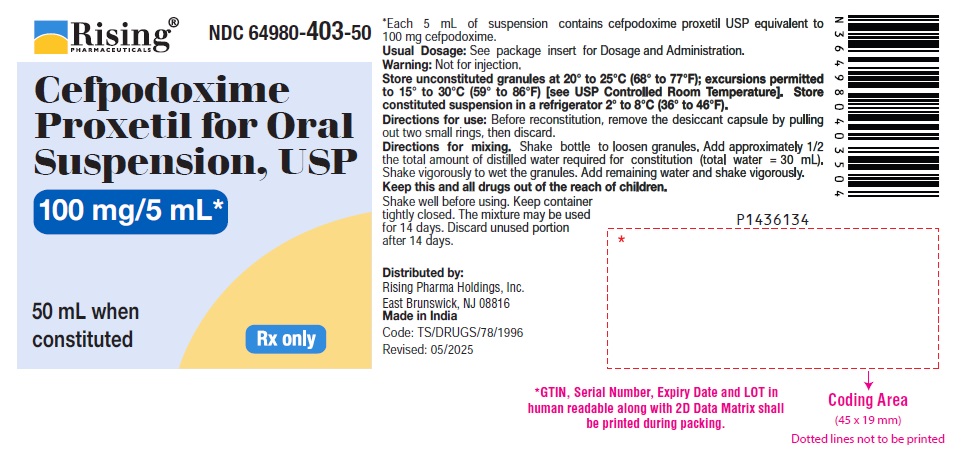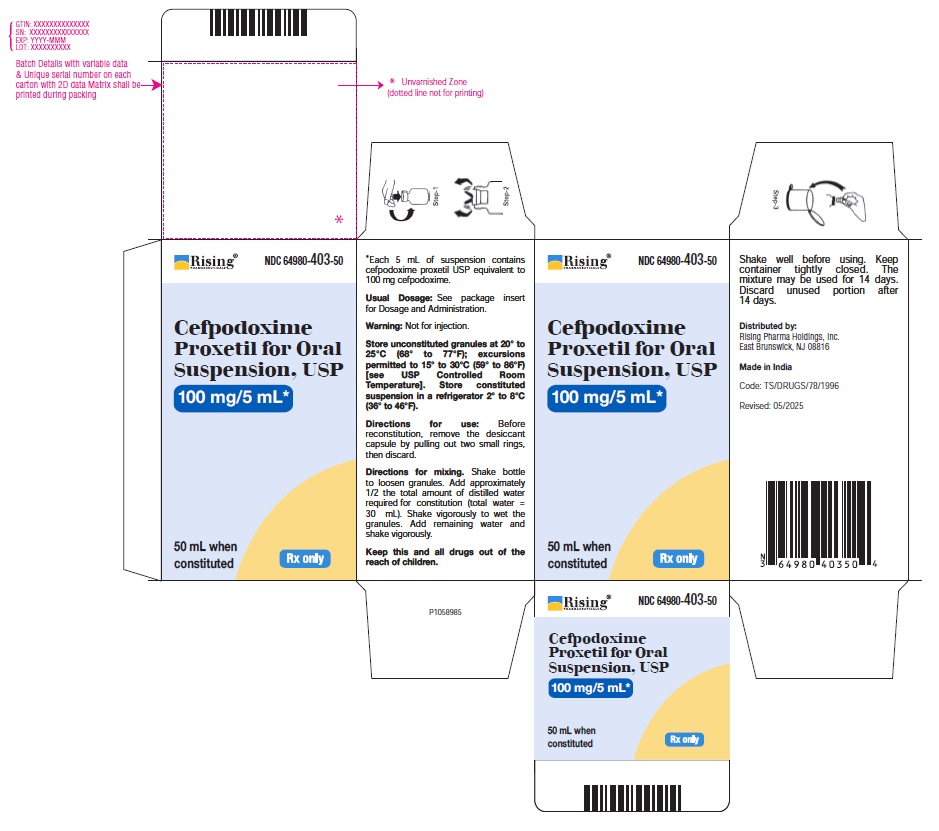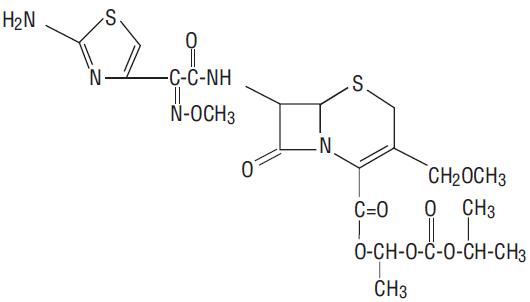 DRUG LABEL: Cefpodoxime Proxetil
NDC: 64980-402 | Form: GRANULE, FOR SUSPENSION
Manufacturer: Rising Pharma Holdings, Inc.
Category: prescription | Type: Human Prescription Drug Label
Date: 20250606

ACTIVE INGREDIENTS: CEFPODOXIME PROXETIL 50 mg/5 mL
INACTIVE INGREDIENTS: LACTOSE MONOHYDRATE; STARCH, CORN; CROSCARMELLOSE SODIUM; FERRIC OXIDE YELLOW; HYDROXYPROPYL CELLULOSE (1600000 WAMW); MICROCRYSTALLINE CELLULOSE; CARBOXYMETHYLCELLULOSE SODIUM; SILICON DIOXIDE; ANHYDROUS CITRIC ACID; TRISODIUM CITRATE DIHYDRATE; SODIUM BENZOATE; SUCROSE

Cefpodoxime Proxetil for Oral Suspension, USP
Rx only

To reduce the development of drug-resistant bacteria and maintain the effectiveness of cefpodoxime proxetil and other antibacterial drugs, cefpodoxime proxetil should be used only to treat or prevent infections that are proven or strongly suspected to be caused by bacteria.
For Oral Use Only

DESCRIPTION

Cefpodoxime proxetil is an orally administered, extended spectrum, semi-synthetic antibiotic of the cephalosporin class. The chemical name is (RS)-1(isopropoxycarbonyloxy) ethyl (+)-(6R,7R)-7-[2-(2-amino-4-thiazolyl)-2-{(Z)methoxyimino}acetamido]-3-methoxymethyl-8-oxo-5-thia-1-azabicyclo [4.2.0]oct-2-ene- 2-carboxylate.
Its molecular formula is C21H27N5O9S2 and its structural formula is represented below:

The molecular weight of cefpodoxime proxetil is 557.6.
Cefpodoxime proxetil is a prodrug; its active metabolite is cefpodoxime. All doses of cefpodoxime proxetil in this insert are expressed in terms of the active cefpodoxime moiety. The drug is supplied as flavoured granules for oral suspension.
Each 5 mL of cefpodoxime proxetil for oral suspension USP contains cefpodoxime proxetil USP equivalent to 50 mg or 100 mg of cefpodoxime activity after constitution and the following inactive ingredients: lactose monohydrate, corn starch, croscarmellose sodium, ferric oxide yellow, hydroxypropyl cellulose, microcrystalline cellulose and carboxymethyl cellulose sodium, colloidal silicon dioxide, citric acid anhydrous, sodium citrate, sodium benzoate, sucrose, and citron & vanille flavorings.

CLINICAL PHARMACOLOGY

Absorption and Excretion:
Cefpodoxime proxetil is a prodrug that is absorbed from the gastrointestinal tract and de-esterified to its active metabolite, cefpodoxime. Following oral administration of 100 mg of cefpodoxime proxetil to fasting subjects, approximately 50% of the administered cefpodoxime dose was absorbed systemically. Over the recommended dosing range (100 to 400 mg), approximately 29 to 33% of the administered cefpodoxime dose was excreted unchanged in the urine in 12 hours. There is minimal metabolism of cefpodoxime in vivo.
Effects of Food:
When a 200 mg dose of the suspension was taken with food, the extent of absorption (mean AUC) and mean peak plasma concentration in fed subjects were not significantly different from fasted subjects, but the rate of absorption was slower with food (48% increase in Tmax).
Pharmacokinetics of Cefpodoxime Proxetil Suspension:
In adult subjects, a 100 mg dose of oral suspension produced an average peak cefpodoxime concentration of approximately 1.5 mcg/mL (range: 1.1 to 2.1 mcg/mL), which is equivalent to that reported following administration of the 100 mg tablet. Time to peak plasma concentration and area under the plasma concentration-time curve (AUC) for the oral suspension were also equivalent to those produced with film-coated tablets in adults following a 100 mg oral dose.
The pharmacokinetics of cefpodoxime were investigated in 29 patients aged 1 to 17 years. Each patient received a single, oral, 5 mg/kg dose of cefpodoxime oral suspension. Plasma and urine samples were collected for 12 hours after dosing. The plasma levels reported from this study are as follows:

CEFPODOXIME PLASMA LEVELS (mcg/mL) IN FASTED PATIENTS (1 to 17 YEARS OF AGE) AFTER SUSPENSION ADMINISTRATION
Dose (cefpodoxime equivalents) | Time after oral ingestion
Dose (cefpodoxime equivalents) | 1hr | 2hr | 3hr | 4hr | 6hr | 8hr | 12hr
5 mg/kg^1 | 1.4 | 2.1 | 2.1 | 1.7 | 0.9 | 0.4 | 0.09
^1 Dose did not exceed 200 mg.

Distribution:
Protein binding of cefpodoxime ranges from 22 to 33% in serum and from 21 to 29% in plasma.
Skin Blister:
Following multiple-dose administration every 12 hours for 5 days of 200 mg or 400 mg cefpodoxime proxetil, the mean maximum cefpodoxime concentration in skin blister fluid averaged 1.6 and 2.8 mcg/mL, respectively. Skin blister fluid cefpodoxime levels at 12 hours after dosing averaged 0.2 and 0.4 mcg/mL for the 200 mg and 400 mg multiple-dose regimens, respectively.
Tonsil Tissue:
Following a single, oral 100 mg cefpodoxime proxetil film-coated tablet, the mean maximum cefpodoxime concentration in tonsil tissue averaged 0.24 mcg/g at 4 hours post-dosing and 0.09 mcg/g at 7 hours post-dosing. Equilibrium was achieved between plasma and tonsil tissue within 4 hours of dosing. No detection of cefpodoxime in tonsillar tissue was reported 12 hours after dosing. These results demonstrated that concentrations of cefpodoxime exceeded the MIC90 of S. pyogenes for at least 7 hours after dosing of 100 mg of cefpodoxime proxetil.
Lung Tissue:
Following a single, oral 200 mg cefpodoxime proxetil film-coated tablet, the mean maximum cefpodoxime concentration in lung tissue averaged 0.63 mcg/g at 3 hours post-dosing, 0.52 mcg/g at 6 hours post-dosing, and 0.19 mcg/g at 12 hours post-dosing. The results of this study indicated that cefpodoxime penetrated into lung tissue and produced sustained drug concentrations for at least 12 hours after dosing at levels that exceeded the MIC90 for S. pneumoniae and H. influenzae.
CSF:
Adequate data on CSF levels of cefpodoxime are not available.
Effects of Decreased Renal Function:
Elimination of cefpodoxime is reduced in patients with moderate to severe renal impairment (<50 mL/min creatinine clearance). (See PRECAUTIONS and DOSAGE AND ADMINISTRATION.) In subjects with mild impairment of renal function (50 to 80 mL/min creatinine clearance), the average plasma half-life of cefpodoxime was 3.5 hours. In subjects with moderate (30 to 49 mL/min creatinine clearance) or severe renal impairment (5 to 29 mL/min creatinine clearance), the half-life increased to 5.9 and 9.8 hours, respectively. Approximately 23% of the administered dose was cleared from the body during a standard 3-hour hemodialysis procedure.
Effect of Hepatic Impairment (cirrhosis):
Absorption was somewhat diminished and elimination unchanged in patients with cirrhosis. The mean cefpodoxime T1/2 and renal clearance in cirrhotic patients were similar to those derived in studies of healthy subjects. Ascites did not appear to affect values in cirrhotic subjects. No dosage adjustment is recommended in this patient population.
Pharmacokinetics in Elderly Subjects:
Elderly subjects do not require dosage adjustments unless they have diminished renal function. (See PRECAUTIONS.) In healthy geriatric subjects, cefpodoxime half-life in plasma averaged 4.2 hours (Vs 3.3 in younger subjects) and urinary recovery averaged 21% after a 400 mg dose was administered every 12 hours. Other pharmacokinetic parameters (Cmax, AUC, and Tmax) were unchanged relative to those observed in healthy young subjects.

Microbiology:

Mechanism of Action:
Cefpodoxime is a bactericidal agent that acts by inhibition of bacterial cell wall synthesis. Cefpodoxime has activity in the presence of some beta-lactamases, both penicillinases and cephalosporinases, of Gram-negative and Gram-positive bacteria.
Mechanism of Resistance:
Resistance to Cefpodoxime is primarily through hydrolysis by beta-lactamase, alteration of penicillin-binding proteins (PBPs), and decreased permeability.
Cefpodoxime has been shown to be active against most isolates of the following bacteria, both in vitro and in clinical infections as described in the Indications and Usage (1) section:
Gram-positive bacteria:
Staphylococcus aureus (methicillin-susceptible strains, including those producing penicillinases)

Staphylococcus saprophyticus

Streptococcus pneumoniae (excluding penicillin-resistant isolates)

Streptococcus pyogenes

Gram-negative bacteria:

Escherichia coli

Klebsiella pneumoniae

Proteus mirabilis

Haemophilus influenzae (including beta-lactamase producing isolates)

Moraxella catarrhalis

Neisseria gonorrhoeae (including penicillinase-producing isolates)

The following in vitro data are available, but their clinical significance is unknown. At least 90 percent of the following microorganisms exhibit an in vitro minimum inhibitory concentration (MIC) less than or equal to the susceptible breakpoint for Cefpodoxime. However, the efficacy of Cefpodoxime in treating clinical infections due to these microorganisms has not been established in adequate and well-controlled clinical trials.

Gram-positive bacteria:

Streptococcus agalactiae

Streptococcus spp. (Groups C, F, G)

Gram-negative bacteria:

Citrobacter diversus

Klebsiella oxytoca

Proteus vulgaris

Providencia rettgeri

Haemophilus parainfluenzae

Anaerobic Gram-positive bacteria:

Peptostreptococcus magnus
Susceptibility Testing:
For specific information regarding susceptibility test interpretive criteria and associated test methods and quality control standards recognized by FDA for this drug, please see: https://www.fda.gov/STIC.

INDICATIONS AND USAGE

Cefpodoxime proxetil is indicated for the treatment of patients with mild to moderate infections caused by susceptible strains of the designated microorganisms in the conditions listed below.
Recommended dosages, durations of therapy, and applicable patient populations vary among these infections. Please see DOSAGE AND ADMINISTRATION for specific recommendations. Acute otitis media caused by Streptococcus pneumoniae (excluding penicillin-resistant strains), Streptococcus pyogenes, Haemophilus influenzae (including beta-lactamase-producing strains), or Moraxella (Branhamella) catarrhalis (including beta-lactamase producing strains).
Pharyngitis and/or tonsillitis caused by Streptococcus pyogenes.
NOTE: Only penicillin by the intramuscular route of administration has been shown to be effective in the prophylaxis of rheumatic fever. Cefpodoxime proxetil is generally effective in the eradication of streptococci from the oropharynx. However, data establishing the efficacy of cefpodoxime proxetil for the prophylaxis of subsequent rheumatic fever are not available.
Community-acquired pneumonia caused by S. pneumoniae or H. Influenzae (including beta-lactamase-producing strains).
Acute bacterial exacerbation of chronic bronchitis caused by S. pneumoniae, H. influenzae (non-beta-lactamase-producing strains only), or M. catarrhalis. Data are insufficient at this time to establish efficacy in patients with acute bacterial exacerbations of chronic bronchitis caused by beta-lactamase-producing strains of H. influenzae.
Acute, uncomplicated urethral and cervical gonorrhea caused by Neisseria gonorrhoeae (including penicillinase-producing strains).
Acute, uncomplicated ano-rectal infections in women due to Neisseria gonorrhoeae (including penicillinase-producing strains).
NOTE: The efficacy of cefpodoxime in treating male patients with rectal infections caused by N. gonorrhoeae has not been established. Data do not support the use of cefpodoxime proxetil in the treatment of pharyngeal infections due to N. gonorrhoeae in men or women.
Uncomplicated skin and skin structure infections caused by Staphylococcus aureus (including penicillinase-producing strains) or Streptococcus pyogenes. Abscesses should be surgically drained as clinically indicated.
NOTE: In clinical trials, successful treatment of uncomplicated skin and skin structure infections was dose-related. The effective therapeutic dose for skin infections was higher than those used in other recommended indications. (See DOSAGE AND ADMINISTRATION.)
Acute maxillary sinusitis caused by Haemophilus influenzae (including beta-lactamase-producing strains), Streptococcus pneumoniae, and Moraxella catarrhalis.
Uncomplicated urinary tract infections (cystitis) caused by Escherichia coli, Klebsiella pneumoniae, Proteus mirabilis, or Staphylococcus saprophyticus.
NOTE: In considering the use of cefpodoxime proxetil in the treatment of cystitis, cefpodoxime proxetil’s lower bacterial eradication rates should be weighed against the increased eradication rates and different safety profiles of some other classes of approved agents. (See CLINICAL STUDIES section.)
Appropriate specimens for bacteriological examination should be obtained in order to isolate and identify causative organisms and to determine their susceptibility to cefpodoxime. Therapy may be instituted while awaiting the results of these studies. Once these results become available, antimicrobial therapy should be adjusted accordingly.
To reduce the development of drug-resistant bacteria and maintain the effectiveness of cefpodoxime proxetil and other antibacterial drugs, cefpodoxime proxetil should be used only to treat or prevent infections that are proven or strongly suspected to be caused by susceptible bacteria. When culture and susceptibility information are available, they should be considered in selecting or modifying antibacterial therapy. In the absence of such data, local epidemiology and susceptibility patterns may contribute to the empiric selection of therapy.

CONTRAINDICATIONS

Cefpodoxime proxetil is contraindicated in patients with a known allergy to cefpodoxime or to the cephalosporin group of antibiotics.

WARNINGS

BEFORE THERAPY WITH CEFPODOXIME PROXETIL IS INSTITUTED, CAREFUL INQUIRY SHOULD BE MADE TO DETERMINE WHETHER THE PATIENT HAS HAD PREVIOUS HYPERSENSITIVITY REACTIONS TO CEFPODOXIME, OTHER CEPHALOSPORINS, PENICILLINS, OR OTHER DRUGS. IF CEFPODOXIME IS TO BE ADMINISTERED TO PENICILLIN SENSITIVE PATIENTS, CAUTION SHOULD BE EXERCISED BECAUSE CROSS HYPERSENSITIVITY AMONG BETA-LACTAM ANTIBIOTICS HAS BEEN CLEARLY DOCUMENTED AND MAY OCCUR IN UP TO 10% OF PATIENTS WITH A HISTORY OF PENICILLIN ALLERGY. IF AN ALLERGIC REACTION TO CEFPODOXIME PROXETIL OCCURS, DISCONTINUE THE DRUG. SERIOUS ACUTE HYPERSENSITIVITY REACTIONS MAY REQUIRE TREATMENT WITH EPINEPHRINE AND OTHER EMERGENCY MEASURES, INCLUDING OXYGEN, INTRAVENOUS FLUIDS, INTRAVENOUS ANTIHISTAMINE, AND AIRWAY MANAGEMENT, AS CLINICALLY INDICATED.
Clostridium difficile associated diarrhea (CDAD) has been reported with use of nearly all antibacterial agents, including cefpodoxime proxetil, and may range in severity from mild diarrhea to fatal colitis. Treatment with antibacterial agents alters the normal flora of the colon leading to overgrowth of C. difficile.
C. difficile produces toxins A and B which contribute to the development of CDAD. Hypertoxin producing strains of C. difficile cause increased morbidity and mortality, as these infections can be refractory to antimicrobial therapy and may require colectomy. CDAD must be considered in all patients who present with diarrhea following antibiotic use. Careful medical history is necessary since CDAD has been reported to occur over two months after the administration of antibacterial agents.
If CDAD is suspected or confirmed, ongoing antibiotic use not directed against C. difficile may need to be discontinued. Appropriate fluid and electrolyte management, protein supplementation, antibiotic treatment of C. difficile, and surgical evaluation should be instituted as clinically indicated.
A concerted effort to monitor for C. difficile in cefpodoxime-treated patients with diarrhea was undertaken because of an increased incidence of diarrhea associated with C. difficile in early trials in normal subjects. C. difficile organisms or toxin was reported in 10% of the cefpodoxime-treated adult patients with diarrhea; however, no specific diagnosis of pseudomembranous colitis was made in these patients.
In post-marketing experience outside the United States, reports of pseudomembranous colitis associated with the use of cefpodoxime proxetil have been received.

PRECAUTIONS

General:

In patients with transient or persistent reduction in urinary output due to renal insufficiency, the total daily dose of cefpodoxime proxetil should be reduced because high and prolonged serum antibiotic concentrations can occur in such individuals following usual doses. Cefpodoxime, like other cephalosporins, should be administered with caution to patients receiving concurrent treatment with potent diuretics. (See DOSAGE AND ADMINISTRATION.)
As with other antibiotics, prolonged use of cefpodoxime proxetil may result in overgrowth of non-susceptible organisms. Repeated evaluation of the patient’s condition is essential. If superinfection occurs during therapy, appropriate measures should be taken.
Prescribing cefpodoxime proxetil in the absence of a proven or strongly suspected bacterial infection or a prophylactic indication is unlikely to provide benefit to the patient and increases the risk of the development of drug-resistant bacteria.

Information for Patients:

Patients should be counseled that antibacterial drugs including cefpodoxime proxetil should only be used to treat bacterial infections. They do not treat viral infections (e.g., the common cold). When cefpodoxime proxetil is prescribed to treat a bacterial infection, patients should be told that although it is common to feel better early in the course of therapy, the medication should be taken exactly as directed. Skipping doses or not completing the full course of therapy may (1) decrease the effectiveness of the immediate treatment and (2) increase the likelihood that bacteria will develop resistance and will not be treatable by cefpodoxime proxetil or other antibacterial drugs in the future.
Diarrhea is a common problem caused by antibiotics which usually ends when the antibiotic is discontinued. Sometimes after starting treatment with antibiotics, patients can develop watery and bloody stools (with or without stomach cramps and fever) even as late as two or more months after having taken the last dose of the antibiotic. If this occurs, patients should contact their physician as soon as possible.

Drug Interactions:

Antacids: Concomitant administration of high doses of antacids (sodium bicarbonate and aluminum hydroxide) or H2 blockers reduces peak plasma levels by 24% to 42% and the extent of absorption by 27% to 32%, respectively. The rate of absorption is not altered by these concomitant medications. Oral anti-cholinergics (e.g., propantheline) delay peak plasma levels (47% increase in Tmax), but do not affect the extent of absorption (AUC).
Probenecid: As with other beta-lactam antibiotics, renal excretion of cefpodoxime was inhibited by probenecid and resulted in an approximately 31% increase in AUC and 20% increase in peak cefpodoxime plasma levels.
Nephrotoxic drugs: Although nephrotoxicity has not been noted when cefpodoxime proxetil was given alone, close monitoring of renal function is advised when cefpodoxime proxetil is administered concomitantly with compounds of known nephrotoxic potential.

Drug/Laboratory Test Interactions:

Cephalosporins, including cefpodoxime proxetil, are known to occasionally induce a positive direct Coombs’ test.

Carcinogenesis, Mutagenesis, Impairment of Fertility:

Long-term animal carcinogenesis studies of cefpodoxime proxetil have not been performed. Mutagenesis studies of cefpodoxime, including the Ames test both with and without metabolic activation, the chromosome aberration test, the unscheduled DNA synthesis assay, mitotic recombination and gene conversion, the forward gene mutation assay and the in vivo micronucleus test, were all negative. No untoward effects on fertility or reproduction were noted when 100 mg/kg/day or less (2 times the human dose based on mg/m^2) was administered orally to rats.

Pregnancy - Teratogenic Effects:

Pregnancy Category B
Cefpodoxime proxetil was neither teratogenic nor embryocidal when administered to rats during organogenesis at doses up to 100 mg/kg/day (2 times the human dose based on mg/m^2) or to rabbits at doses up to 30 mg/kg/day (1 to 2 times the human dose based on mg/m^2).
There are, however, no adequate and well-controlled studies of cefpodoxime proxetil use in pregnant women. Because animal reproduction studies are not always predictive of human response, this drug should be used during pregnancy only if clearly needed.

Labor and Delivery:

Cefpodoxime proxetil has not been studied for use during labor and delivery. Treatment should only be given if clearly needed.

Nursing Mothers:

Cefpodoxime is excreted in human milk. In a study of 3 lactating women, levels of cefpodoxime in human milk were 0%, 2% and 6% of concomitant serum levels at 4 hours following a 200 mg oral dose of cefpodoxime proxetil. At 6 hours post-dosing, levels were 0%, 9% and 16% of concomitant serum levels. Because of the potential for serious reactions in nursing infants, a decision should be made whether to discontinue nursing or to discontinue the drug, taking into account the importance of the drug to the mother.

Pediatric Use:

Safety and efficacy in infants less than 2 months of age have not been established.

Geriatric Use:

Of the 3338 patients in multiple-dose clinical studies of cefpodoxime proxetil film-coated tablets, 521 (16%) were 65 and over, while 214 (6%) were 75 and over. No overall differences in effectiveness or safety were observed between the elderly and younger patients. In healthy geriatric subjects with normal renal function, cefpodoxime half-life in plasma averaged 4.2 hours and urinary recovery averaged 21% after a 400 mg dose was given every 12 hours for 15 days. Other pharmacokinetic parameters were unchanged relative to those observed in healthy younger subjects.
Dose adjustment in elderly patients with normal renal function is not necessary.

ADVERSE REACTIONS

Clinical Trials:

In clinical trials using multiple doses of cefpodoxime proxetil granules for oral suspension, 2128 pediatric patients (93% of whom were less than 12 years of age) were treated with the recommended dosages of cefpodoxime (10 mg/kg/day Q 24 hours or divided Q 12 hours to a maximum equivalent adult dose). There were no deaths or permanent disabilities in any of the patients in these studies. Twenty-four patients (1.1%) discontinued medication due to adverse events thought possibly or probably related to study drug. Primarily, these discontinuations were for gastrointestinal disturbances, usually diarrhea, vomiting, or rashes.
Adverse events thought possibly or probably related, or of unknown relationship to cefpodoxime proxetil for oral suspension in multiple dose clinical trials (N=2128 patients treated with cefpodoxime) were:
Incidence Greater Than 1%:
Diarrhea 6 %
The incidence of diarrhea in infants and toddlers (age 1 month to 2 years) was 12.8%.
Diaper rash/Fungal skin rash 2 % (includes moniliasis)
The incidence of diaper rash in infants and toddlers was 8.5%.
Other skin rashes 1.8%

Vomiting 2.3%
Incidence Less Than 1%:
Body: Localized abdominal pain, abdominal cramp, headache, monilia, generalized abdominal pain, asthenia, fever, fungal infection.
Digestive: Nausea, monilia, anorexia, dry mouth, stomatitis, pseudomembranous colitis.
Hemic & Lymphatic: Thrombocythemia, positive direct Coombs’ test, eosinophilia, leukocytosis, leukopenia, prolonged partial thromboplastin time, thrombocytopenic purpura.
Metabolic & Nutritional: Increased SGPT.
Musculo-Skeletal: Myalgia.
Nervous: Hallucination, hyperkinesia, nervousness, somnolence.
Respiratory: Epistaxis, rhinitis.
Skin: Skin moniliasis, urticaria, fungal dermatitis, acne, exfoliative dermatitis, maculopapular rash.
Special Senses: Taste perversion.

Laboratory Changes

Significant laboratory changes that have been reported in adult and pediatric patients in clinical trials of cefpodoxime proxetil, without regard to drug relationship, were:
Hepatic: Transient increases in AST (SGOT), ALT (SGPT), GGT, alkaline phosphatase, bilirubin, and LDH.
Hematologic: Eosinophilia, leukocytosis, lymphocytosis, granulocytosis, basophilia, monocytosis, thrombocytosis, decreased hemoglobin, decreased hematocrit, leukopenia, neutropenia, lymphocytopenia, thrombocytopenia, thrombocythemia, positive Coombs’ test, and prolonged PT, and PTT.
Serum Chemistry: Hyperglycemia, hypoglycemia, hypoalbuminemia, hypoproteinemia, hyperkalemia, and hyponatremia.
Renal: Increases in BUN and creatinine.
Most of these abnormalities were transient and not clinically significant.
Post-marketing Experience:
The following serious adverse experiences have been reported: allergic reactions including Stevens-Johnson syndrome, toxic epidermal necrolysis, erythema multiforme and serum sickness-like reactions, pseudomembranous colitis, bloody diarrhea with abdominal pain, ulcerative colitis, rectorrhagia with hypotension, anaphylactic shock, acute liver injury, in utero exposure with miscarriage, purpuric nephritis, pulmonary infiltrate with eosinophilia, and eyelid dermatitis.

One death was attributed to pseudomembranous colitis and disseminated intravascular coagulation.
Cephalosporin Class Labeling:
In addition to the adverse reactions listed above which have been observed in patients treated with cefpodoxime proxetil, the following adverse reactions and altered laboratory tests have been reported for cephalosporin class antibiotics:
Adverse Reactions and Abnormal Laboratory Tests: Renal dysfunction, toxic nephropathy, hepatic dysfunction including cholestasis, aplastic anemia, hemolytic anemia, serum sickness-like reaction, hemorrhage, agranulocytosis, and pancytopenia.
Several cephalosporins have been implicated in triggering seizures, particularly in patients with renal impairment when the dosage was not reduced. (See DOSAGE AND ADMINISTRATION and OVERDOSAGE.) If seizures associated with drug therapy occur, the drug should be discontinued. Anticonvulsant therapy can be given if clinically indicated.

OVERDOSAGE

In acute rodent toxicity studies, a single 5 g/kg oral dose produced no adverse effects.
In the event of serious toxic reaction from overdosage, hemodialysis or peritoneal dialysis may aid in the removal of cefpodoxime from the body, particularly if renal function is compromised.
The toxic symptoms following an overdose of beta-lactam antibiotics may include nausea, vomiting, epigastric distress, and diarrhea.

DOSAGE AND ADMINISTRATION

(See INDICATIONS AND USAGE for indicated pathogens.)
Cefpodoxime proxetil for oral suspension may be given without regard to food. The recommended dosages, durations of treatment, and applicable patient populations are as described in the following chart:

Adults and Adolescents (age 12 years and older):
Type of Infection | Total Daily Dose | Dose Frequency | Duration
Pharyngitis and/or tonsillitis | 200 mg | 100 mg Q 12 hours | 5 to 10 days
Acute community-acquired pneumonia | 400 mg | 200 mg Q 12 hours | 14 days
Uncomplicated gonorrhea (men and women) and rectal gonococcal infections (women) | 200 mg | single dose
Skin and skin structure | 800 mg | 400 mg Q 12 hours | 7 to 14 days
Acute maxillary sinusitis | 400 mg | 200 mg Q 12 hours | 10 days
Uncomplicated urinary tract infection | 200 mg | 100 mg Q 12 hours | 7 days

Infants and Pediatric Patients (age 2 months through 12 years):
Type of Infection | Total Daily Dose | Dose Frequency | Duration
Acute otitis media | 10 mg/kg/day (Max 400 mg/day) | 5 mg/kg Q 12 h (Max 200 mg/dose) | 5 days
Pharyngitis and/or tonsillitis | 10 mg/kg/day (Max 200 mg/day) | 5 mg/kg/dose Q 12 h (Max 100 mg/dose) | 5 to 10 days
Acute maxillary sinusitis | 10 mg/kg/day (Max 400 mg/day) | 5 mg/kg Q 12 hours (Max 200 mg/dose) | 10 days

Patients with Renal Dysfunction:

For patients with severe renal impairment (<30 mL/min creatinine clearance), the dosing intervals should be increased to Q 24 hours. In patients maintained on hemodialysis, the dose frequency should be 3 times/week after hemodialysis.
When only the serum creatinine level is available, the following formula (based on sex, weight, and age of the patient) may be used to estimate creatinine clearance (mL/min). For this estimate to be valid, the serum creatinine level should represent a steady state of renal function.
Males: Weight (kg) x (140 - age)
(mL/min) 72 x serum creatinine (mg/100 mL)
Females: 0.85 x above value
(mL/min)

Patients with Cirrhosis:

Cefpodoxime pharmacokinetics in cirrhotic patients (with or without ascites) are similar to those in healthy subjects. Dose adjustment is not necessary in this population.

Directions for use:

Before reconstitution, remove the desiccant capsule by pulling out two small rings, then discard.

Preparation of Suspension:

Constitution Directions For Oral Suspension
Constituted Volume | Final Concentration | Directions
50 mL | 50 mg per 5 mL | Suspend in a total of 31 mL of distilled water. Method: First, shake the bottle to loosen granules. Then add the water in two approximately equal portions, shaking vigorously after each aliquot of water.
75 mL | 50 mg per 5 mL | Suspend in a total of 44 mL of distilled water. Method: First, shake the bottle to loosen granules. Then add the water in two approximately equal portions, shaking vigorously after each aliquot of water.
100 mL | 50 mg per 5 mL | Suspend in a total of 57 mL of distilled water. Method: First, shake the bottle to loosen granules. Then add the water in two approximately equal portions, shaking vigorously after each aliquot of water.
50 mL | 100 mg per 5 mL | Suspend in a total of 30 mL of distilled water. Method: First, shake the bottle to loosen granules. Then add the water in two approximately equal portions, shaking vigorously after each aliquot of water.
75 mL | 100 mg per 5 mL | Suspend in a total of 43 mL of distilled water. Method: First, shake the bottle to loosen granules. Then add the water in two approximately equal portions, shaking vigorously after each aliquot of water.
100 mL | 100 mg per 5 mL | Suspend in a total of 57 mL of distilled water. Method: First, shake the bottle to loosen granules. Then add the water in two approximately equal portions, shaking vigorously after each aliquot of water.

After mixing, the suspension should be stored in a refrigerator, 2° to 8°C (36° to 46°F). Shake well before using. Keep container tightly closed. The mixture may be used for 14 days. Discard unused portion after 14 days.

HOW SUPPLIED

Cefpodoxime Proxetil for Oral Suspension, USP provides the equivalent of 50 mg or 100 mg cefpodoxime per 5 mL suspension (when constituted as directed) and is available as off-white colored granular powder in the following sizes:
50 mg/5 mL
50-mL suspension NDC 64980-402-50
100-mL suspension NDC 64980-402-10
100 mg/5 mL
50-mL suspension NDC 64980-403-50
100-mL suspension NDC 64980-403-10
Store unsuspended granules at 20° to 25°C (68° to 77°F); excursions permitted to 15° to 30°C (59° to 86°F) [see USP Controlled Room Temperature].
Directions for mixing are included on the label. After mixing, suspension should be stored in a refrigerator, 2° to 8°C (36° to 46°F). Shake well before using. Keep container tightly closed. The mixture may be used for 14 days. Discard unused portion after 14 days.

CLINICAL TRIALS

Cystitis
In two double-blind, 2:1 randomized, comparative trials performed in adults in the United States, cefpodoxime proxetil was compared to other beta-lactam antibiotics. In these studies, the following bacterial eradication rates were obtained at 5 to 9 days after therapy:

Pathogen | Cefpodoxime | Comparator
E. coli | 200/243 (82%) | 99/123 (80%)
Other pathogens | 34/42 (81%) | 23/28 (82%)
K. pneumoniae P. mirabilis S. saprophyticus
TOTAL | 234/285 (82%) | 122/151 (81%)

In these studies, clinical cure rates and bacterial eradication rates for cefpodoxime proxetil were comparable to the comparator agents; however, the clinical cure rates and bacteriologic eradication rates were lower than those observed with some other classes of approved agents for cystitis.
Acute Otitis Media Studies
In controlled studies of acute otitis media performed in the United States, where significant rates of beta-lactamase-producing organisms were found, cefpodoxime proxetil was compared to cefixime. In these studies, using very strict evaluability criteria and microbiologic and clinical response criteria at the 4 to 21 day post-therapy follow-up, the following presumptive bacterial eradication/clinical success outcomes (cured and improved) were obtained.

 | Cefpodoxime Proxetil | Cefixime
Pathogen | 5 mg/kg Q 12 h x 5 d
S. pneumoniae | 88/122 (72%) | 72/124 (58%)
H. influenzae | 50/76 (66%) | 61/81 (75%)
M. catarrhalis | 22/39 (56%) | 23/41 (56%)
S. pyogenes | 20/25 (80%) | 13/23 (57%)
Clinical success rate | 171/254 (67%) | 165/258 (64%)

Distributed by:
Rising Pharma Holdings, Inc.
East Brunswick, NJ 08816
Made in India
Code: TS/DRUGS/78/1996
Revised: 05/2025

PACKAGE LABEL-PRINCIPAL DISPLAY PANEL - 50 mg/5 mL (50 mL Bottle)

Rising® NDC 64980-402-50

PHARMACEUTICALS

Cefpodoxime
Proxetil for Oral
Suspension, USP
50 mg/5 mL*
50 mL when
constituted Rx only

PACKAGE LABEL-PRINCIPAL DISPLAY PANEL - 50 mg/5 mL (50 mL Carton Label)

Rising® NDC 64980-402-50

PHARMACEUTICALS

Cefpodoxime
Proxetil for Oral
Suspension, USP
50 mg/5 mL*
50 mL when
constituted Rx only

PACKAGE LABEL-PRINCIPAL DISPLAY PANEL - 100 mg/5 mL (50 mL Bottle)

Rising® NDC 64980-403-50

PHARMACEUTICALS

Cefpodoxime
Proxetil for Oral
Suspension, USP

100 mg/5 mL*
50 mL when
constituted Rx only

PACKAGE LABEL-PRINCIPAL DISPLAY PANEL - 100 mg/5 mL (50 mL Carton Label)

Rising® NDC 64980-403-50

PHARMACEUTICALS

Cefpodoxime
Proxetil for Oral
Suspension, USP

100 mg/5 mL*
50 mL when
constituted Rx only